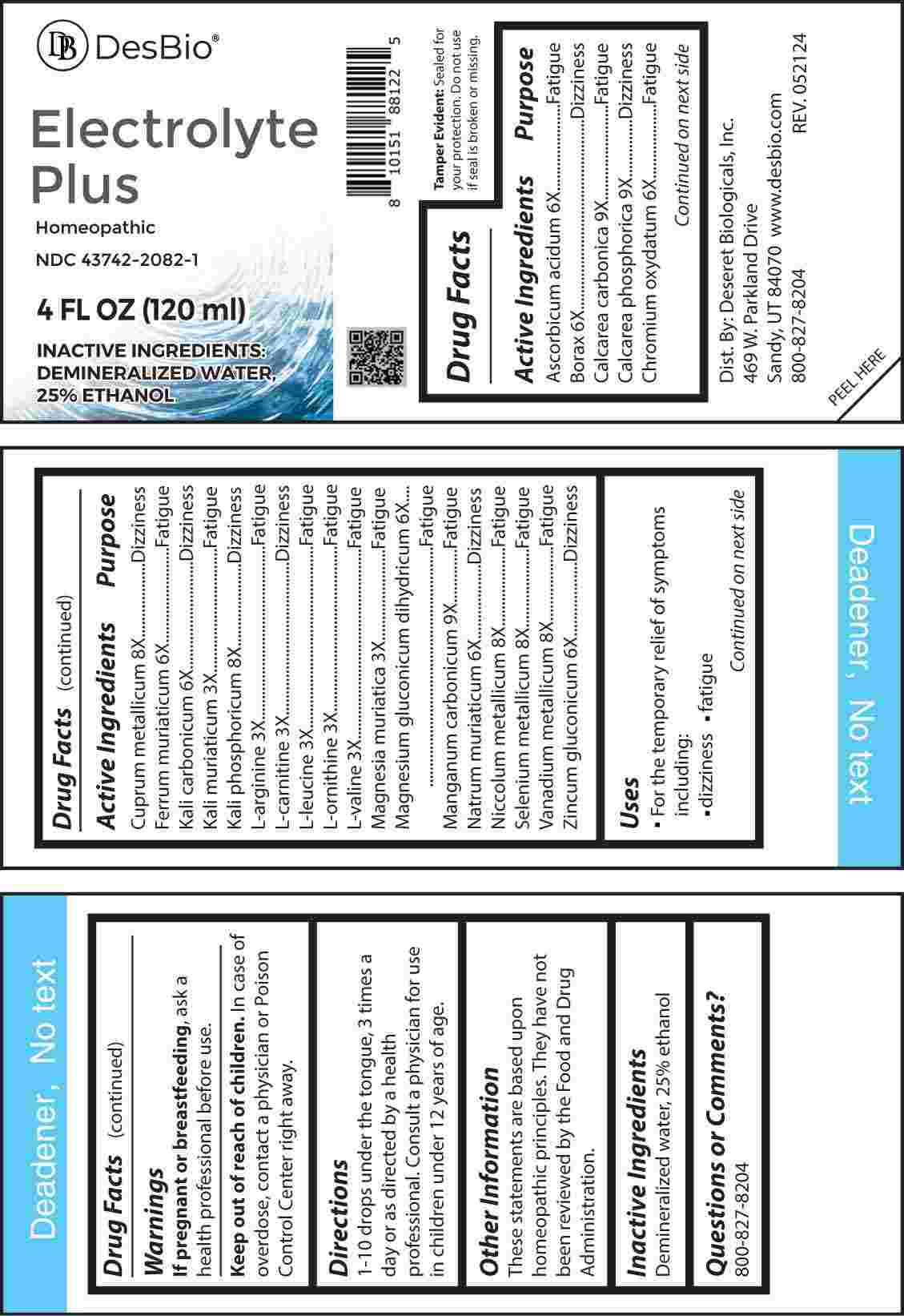 DRUG LABEL: Electrolyte Plus
NDC: 43742-2082 | Form: LIQUID
Manufacturer: Deseret Biologicals, Inc.
Category: homeopathic | Type: HUMAN OTC DRUG LABEL
Date: 20240924

ACTIVE INGREDIENTS: POTASSIUM CHLORIDE 3 [hp_X]/1 mL; ARGININE 3 [hp_X]/1 mL; LEVOCARNITINE 3 [hp_X]/1 mL; LEUCINE 3 [hp_X]/1 mL; ORNITHINE 3 [hp_X]/1 mL; VALINE 3 [hp_X]/1 mL; MAGNESIUM CHLORIDE 3 [hp_X]/1 mL; ASCORBIC ACID 6 [hp_X]/1 mL; SODIUM BORATE 6 [hp_X]/1 mL; CHROMIC OXIDE 6 [hp_X]/1 mL; FERRIC CHLORIDE HEXAHYDRATE 6 [hp_X]/1 mL; POTASSIUM CARBONATE 6 [hp_X]/1 mL; MAGNESIUM GLUCONATE 6 [hp_X]/1 mL; SODIUM CHLORIDE 6 [hp_X]/1 mL; ZINC GLUCONATE 6 [hp_X]/1 mL; COPPER 8 [hp_X]/1 mL; DIBASIC POTASSIUM PHOSPHATE 8 [hp_X]/1 mL; NICKEL 8 [hp_X]/1 mL; SELENIUM 8 [hp_X]/1 mL; VANADIUM 8 [hp_X]/1 mL; OYSTER SHELL CALCIUM CARBONATE, CRUDE 9 [hp_X]/1 mL; TRIBASIC CALCIUM PHOSPHATE 9 [hp_X]/1 mL; MANGANESE CARBONATE 9 [hp_X]/1 mL
INACTIVE INGREDIENTS: WATER; ALCOHOL

DRUG FACTS:

ACTIVE INGREDIENTS:

Ascorbicum Acidum 6X, Borax 6X, Calcarea Carbonica 9X, Calcarea Phosphorica 9X, Chromium Oxydatum 6X, Cuprum Metallicum 8X, Ferrum Muriaticum 6X, Kali Carbonicum 6X, Kali Muriaticum 3X, Kali Phosphoricum 8X, L-Arginine 3X, L-Carnitine 3X, L-Leucine 3X, L-Ornithine 3X, L-Valine 3X, Magnesia Muriatica 3X, Magnesium Gluconicum Dihydricum 6X, Manganum Carbonicum 9X, Natrum Muriaticum 6X, Niccolum Metallicum 8X, Selenium Metallicum 8X, Vanadium Metallicum 8X, Zincum Gluconicum 6X.

PURPOSE:

Ascorbicum Acidum - Fatigue, Borax - Dizziness, Calcarea Carbonica - Fatigue, Calcarea Phosphorica - Dizziness, Chromium Oxydatum - Fatigue, Cuprum Metallicum - Dizziness, Ferrum Muriaticum - Fatigue, Kali Carbonicum - Dizziness, Kali Muriaticum - Fatigue, Kali Phosphoricum - Dizziness, L-Arginine - Fatigue, L-Carnitine - Dizziness, L-Leucine - Fatigue, L-Ornithine - Fatigue, L-Valine - Fatigue, Magnesia Muriatica - Fatigue, Magnesium Gluconicum Dihydricum - Fatigue, Manganum Carbonicum - Fatigue, Natrum Muriaticum - Dizziness, Niccolum Metallicum - Fatigue, Selenium Metallicum - Fatigue, Vanadium Metallicum - Fatigue, Zincum Gluconicum - Dizziness

USES:

• For the temporary relief of symptoms including:

• dizziness • fatigue

These statements are based upon homeopathic principles. They have not been reviewed by the Food and Drug Administration.

WARNINGS:

If pregnant or breast-feeding, ask a health professional before use.

Keep out of reach of children. In case of overdose, contact a physician or Poison Control Center right away.

Tamper Evident: Sealed for your protection. Do not use if seal is broken or missing.

KEEP OUT OF REACH OF CHILDREN:

In case of overdose, contact a physician or Poison Control Center right away.

DIRECTIONS:

1-10 drops under the tongue, 3 times a day or as directed by a health professional. Consult a physician for use in children under 12 years of age.

INACTIVE INGREDIENTS:

Demineralized water, 25% ethanol

QUESTIONS:

Dist. By: Deseret Biologicals, Inc.

469 W. Parkland Drive

Sandy, UT 84070

www.desbio.com

800-827-8204

PACKAGE LABEL DISPLAY:

DesBio

Electrolyte Plus

Homeopathic

NDC 43742-2082-1

4 FL OZ (120 ml)